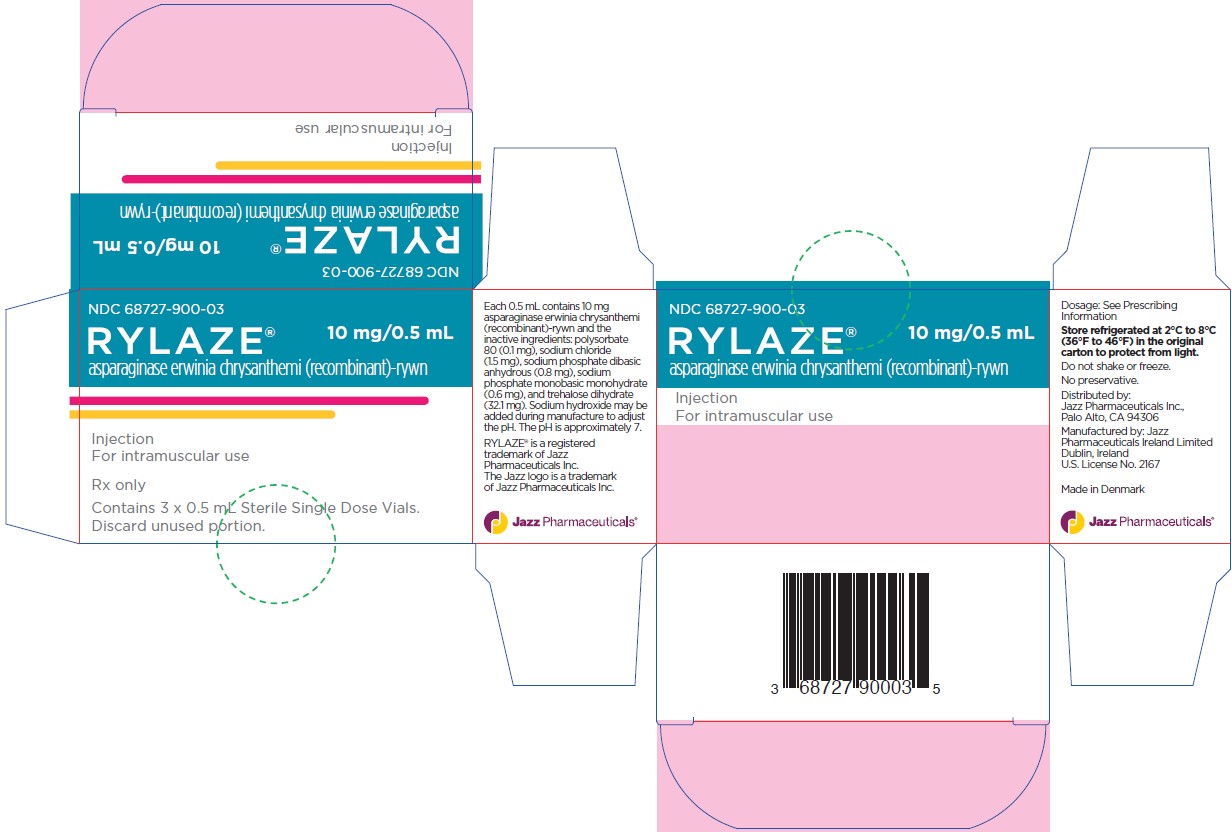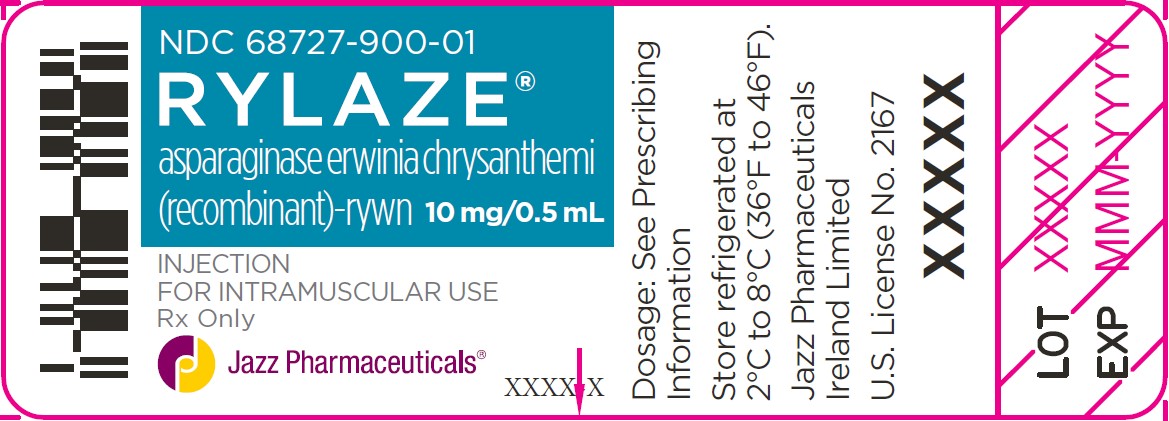 DRUG LABEL: Rylaze
NDC: 68727-900 | Form: INJECTION
Manufacturer: Jazz Pharmaceuticals, Inc.
Category: prescription | Type: HUMAN PRESCRIPTION DRUG LABEL
Date: 20250701

ACTIVE INGREDIENTS: ASPARAGINASE 20 mg/1 mL
INACTIVE INGREDIENTS: TREHALOSE DIHYDRATE 170 mmol/1 mL; SODIUM CHLORIDE 50 mmol/1 mL; SODIUM PHOSPHATE, DIBASIC, ANHYDROUS 11.6 mmol/1 mL; SODIUM PHOSPHATE, MONOBASIC, MONOHYDRATE 8.5 mmol/1 mL; POLYSORBATE 80 0.2 mg/1 mL

HIGHLIGHTS OF PRESCRIBING INFORMATION

These highlights do not include all the information needed to use RYLAZE safely and effectively. See full prescribing information for RYLAZE.
RYLAZE® (asparaginase erwinia chrysanthemi (recombinant)-rywn) injection, for intramuscular use
Initial U.S. Approval: 2021

1 INDICATIONS AND USAGE

RYLAZE is an asparagine specific enzyme indicated as a component of a multi-agent chemotherapeutic regimen for the treatment of acute lymphoblastic leukemia (ALL) and lymphoblastic lymphoma (LBL) in adult and pediatric patients 1 month or older who have developed hypersensitivity to E. coli-derived asparaginase. (1)

2 DOSAGE AND ADMINISTRATION

There are two RYLAZE regimens that can be used to replace a long-acting asparaginase product. The recommended dosages of RYLAZE are:

When administered every 48 hours

- 25 mg/m^2 intramuscularly every 48 hours;

When administered Monday/Wednesday/Friday

- 25 mg/m^2 intramuscularly on Monday morning and Wednesday morning and 50 mg/m^2 intramuscularly on Friday afternoon. (2.1)

3 DOSAGE FORMS AND STRENGTHS

Injection: 10 mg/0.5 mL solution in a single-dose vial. (3)

4 CONTRAINDICATIONS

RYLAZE is contraindicated in patients with:

- History of serious hypersensitivity reactions to RYLAZE, including anaphylaxis. (4)
- History of serious pancreatitis during previous L-asparaginase therapy. (4)
- History of serious thrombosis during previous L-asparaginase therapy. (4)
- History of serious hemorrhagic events during previous L-asparaginase therapy. (4)
- Severe hepatic impairment. (4)

5 WARNINGS AND PRECAUTIONS

- Hypersensitivity: Monitor for signs or symptoms. Discontinue RYLAZE for serious reaction. (5.1)
- Pancreatitis: Monitor for symptoms. Discontinue if pancreatitis occurs. (5.2)
- Thrombosis: Discontinue RYLAZE for severe or life-threatening thrombosis. Provide anticoagulation therapy as indicated. (5.3)
- Hemorrhage: Discontinue RYLAZE for severe or life-threatening hemorrhage. (5.4)
- Hepatotoxicity, including hepatic veno-occlusive disease: Discontinue RYLAZE for grade 4 increases of bilirubin. (5.5)

6 ADVERSE REACTIONS

Most common adverse reactions (incidence > 20%) are abnormal liver test, nausea, musculoskeletal pain, infection, fatigue, headache, febrile neutropenia, pyrexia, hemorrhage, stomatitis, abdominal pain, decreased appetite, drug hypersensitivity, hyperglycemia, diarrhea, pancreatitis, and hypokalemia. (6.1)

To report SUSPECTED ADVERSE REACTIONS, contact Jazz Pharmaceuticals Ireland Limited at 1-800-520-5568 or FDA at 1-800-FDA-1088 or www.fda.gov/medwatch.

8 USE IN SPECIFIC POPULATIONS

- Lactation: Advise not to breastfeed. (8.2)

FULL PRESCRIBING INFORMATION

1 INDICATIONS AND USAGE

RYLAZE is indicated as a component of a multi-agent chemotherapeutic regimen for the treatment of acute lymphoblastic leukemia (ALL) and lymphoblastic lymphoma (LBL) in adult and pediatric patients 1 month or older who have developed hypersensitivity to E. coli-derived asparaginase.

2 DOSAGE AND ADMINISTRATION

2.1 Recommended Dosage

There are two RYLAZE regimens that can be used to replace a long-acting asparaginase product. The recommended dosages of RYLAZE are:

When administered every 48 hours:

- 25 mg/m^2 administered intramuscularly every 48 hours;

When administered on a Monday/Wednesday/Friday schedule:

- 25 mg/m^2 intramuscularly on Monday morning and Wednesday morning, and 50 mg/m^2 intramuscularly on Friday afternoon. Administer the Friday afternoon dose 53 to 58 hours after the Wednesday morning dose (e.g., 8:00 am on Monday and Wednesday, and 1:00 pm to 6:00 pm on Friday) [see Clinical Pharmacology (12.3), Clinical Studies (14)].

Table 1 shows the number of RYLAZE dosages recommended for the intended duration of treatment for replacement of one dose of calaspargase pegol products (3 weeks of asparaginase coverage) or one dose of pegaspargase products (2 weeks of asparaginase coverage). See the full prescribing information for the long-acting asparaginase product to determine the total duration of administration of RYLAZE as replacement therapy.

Table 1: Recommended Duration of RYLAZE Dosing to Replace One Long-Acting Asparaginase Dose
When RYLAZE is Administered: | Recommended Duration of RYLAZE to Replace Calaspargase Pegol Products | Recommended Duration of RYLAZE to Replace Pegaspargase Products
25 mg/m^2 intramuscular every 48 hours | Replace one dose of calaspargase pegol products with 11 doses of RYLAZE | Replace one dose of pegaspargase products with 7 doses of RYLAZE
25 mg/m^2 intramuscular on Monday morning and Wednesday morning, and 50 mg/m^2 intramuscular on Friday afternoon* | Replace one dose of calaspargase pegol products with 9 doses of RYLAZE | Replace one dose of pegaspargase products with 6 doses of RYLAZE

*See bullet above for timing of 25/25/50 mg/m^2 dosing of RYLAZE.

2.2 Recommended Premedication

Premedicate patients with acetaminophen, an H-1 receptor blocker (such as diphenhydramine), and an H-2 receptor blocker (such as famotidine) 30-60 minutes prior to administration of RYLAZE to decrease the risk and severity of hypersensitivity reactions [see Warnings and Precautions (5.1)].

2.3 Recommended Monitoring and Dosage Modifications for Adverse Reactions

Monitor patient’s bilirubin, transaminases, glucose, and clinical examinations prior to treatment every 2-3 weeks and as indicated clinically. If results are abnormal, monitor patients until recovery from the cycle of therapy. If an adverse reaction occurs, modify treatment according to Table 2.

Table 2: Dosage Modifications
Adverse Reaction | Severity* | Action
Hypersensitivity Reaction [see Warnings and Precautions (5.1)] | Grade 2 | - Treat the symptoms.
Hypersensitivity Reaction [see Warnings and Precautions (5.1)] | Grade 3 to 4 | - Discontinue RYLAZE permanently.
Pancreatitis [see Warnings and Precautions (5.2)] | Grade 2 to 4 | - Hold RYLAZE for elevations in lipase or amylase > 2 times the ULN**, or for symptomatic pancreatitis. - Resume treatment when lipase and amylase are < 1.5 times the ULN and symptoms are resolved. - Discontinue RYLAZE permanently if clinical necrotizing or hemorrhagic pancreatitis is confirmed.
Thrombosis [see Warnings and Precautions (5.3)] | Uncomplicated thrombosis | - Hold RYLAZE. - Treat with appropriate antithrombotic therapy. - Upon resolution of symptoms, consider resuming RYLAZE, while continuing antithrombotic therapy.
Thrombosis [see Warnings and Precautions (5.3)] | Severe or life-threatening thrombosis | - Discontinue RYLAZE permanently. - Treat with appropriate antithrombotic therapy.
Hemorrhage [see Warnings and Precautions (5.4)] | Grade 3 to 4 | - Hold RYLAZE. - Evaluate for coagulopathy and consider clotting factor replacement as needed. - Resume RYLAZE with the next scheduled dose if bleeding is controlled.
Hepatotoxicity [see Warnings and Precautions (5.5)] | Total bilirubin > 3 times to ≤ 10 times the ULN | - Hold RYLAZE until total bilirubin levels decrease to ≤ 1.5 times the ULN.
Hepatotoxicity [see Warnings and Precautions (5.5)] | Total bilirubin > 10 times the ULN | - Discontinue RYLAZE and do not make up missed doses.

* Common Terminology Criteria for Adverse Events (CTCAE) version 5.0.
** Upper limit of normal

2.4 Preparation and Administration Instructions

Ensure that medical support is available to appropriately manage anaphylactic reactions when administering RYLAZE [see Warnings and Precautions (5.1)].

Parenteral drug products should be inspected visually for particulate matter and discoloration prior to administration, whenever solution and container permit. If particulate matter, cloudiness, or discoloration are present, discard the vial.

- Use aseptic technique.
- Determine the dose, total volume of RYLAZE solution required, and the number of RYLAZE vials needed based on the individual patient’s BSA. More than one vial may be needed for a full dose.
- Withdraw the indicated injection volume of RYLAZE into the syringe for injection.
  - Do not shake the vial.
  - Limit the volume of RYLAZE at a single injection site to 2 mL.
  - If the volume to be administered is greater than 2 mL, divide the doses equally into multiple syringes, one for each injection site.
  - Discard the remaining unused RYLAZE in the single-dose vial.
- Administer RYLAZE by intramuscular injection.
  - Rotate injection sites.
  - Do not inject RYLAZE into scar tissue or areas that are reddened, inflamed, or swollen.
- If the prepared dose is not used immediately, store the syringe(s) at room temperature 15°C to 25°C (59°F to 77°F) for up to 8 hours or refrigerated at 2°C to 8°C (36°F to 46°F) for up to 24 hours. The syringe does not need to be protected from light during storage.

3 DOSAGE FORMS AND STRENGTHS

Injection: 10 mg/0.5 mL clear to opalescent, colorless to slightly yellow solution in a single-dose vial.

4 CONTRAINDICATIONS

RYLAZE is contraindicated in patients with:

- History of serious hypersensitivity reactions to Erwinia asparaginase, including anaphylaxis [see Warnings and Precautions (5.1)];
- History of serious pancreatitis during previous asparaginase therapy [see Warnings and Precautions (5.2)];
- History of serious thrombosis during previous asparaginase therapy [see Warnings and Precautions (5.3)];
- History of serious hemorrhagic events during previous asparaginase therapy [see Warnings and Precautions (5.4)];
- Severe hepatic impairment [see Warnings and Precautions (5.5)].

5 WARNINGS AND PRECAUTIONS

5.1 Hypersensitivity Reactions

Hypersensitivity reactions after the use of RYLAZE occurred in 29% of patients in clinical trials, and it was severe in 6% of patients [see Adverse Reactions (6.1)]. Anaphylaxis was observed in 2% of patients after intramuscular administration. Discontinuation of RYLAZE due to hypersensitivity reactions occurred in 5% of patients. Hypersensitivity reactions were higher in patients who received intravenous asparaginase erwinia chrysanthemi (recombinant)-rywn. The intravenous route of administration is not approved.

In patients administered RYLAZE intramuscularly in clinical trials, the median number of doses of RYLAZE that patients received prior to the onset of the first hypersensitivity reaction was 12 doses (range: 1-64 doses). The most commonly observed reaction was rash (19%), and 1 patient (1%) experienced a severe rash.

Hypersensitivity reactions observed with L-asparaginase class products include angioedema, urticaria, lip swelling, eye swelling, rash or erythema, blood pressure decreased, bronchospasm, dyspnea, and pruritus.

Premedicate patients prior to administration of RYLAZE as recommended [see Dosage and Administration (2.2)]. Because of the risk of serious allergic reactions (e.g., life-threatening anaphylaxis), administer RYLAZE in a setting with resuscitation equipment and other agents necessary to treat anaphylaxis (e.g., epinephrine, oxygen, intravenous steroids, antihistamines) [see Dosage and Administration (2.3)]. Discontinue RYLAZE in patients with serious hypersensitivity reactions [see Dosage and Administration (2.3)].

5.2 Pancreatitis

Pancreatitis, including elevated amylase or lipase, was reported in 20% of patients in clinical trials of RYLAZE and was severe in 8% [see Adverse Reactions (6.1)]. Symptomatic pancreatitis occurred in 7% of patients, and it was severe in 6% of patients. Elevated amylase or lipase without symptomatic pancreatitis was observed in 13% of patients treated with RYLAZE. Hemorrhagic or necrotizing pancreatitis have been reported with L-asparaginase class products.

Inform patients of the signs and symptoms of pancreatitis, which, if left untreated, could be fatal. Evaluate patients with symptoms compatible with pancreatitis to establish a diagnosis. Assess serum amylase and lipase levels in patients with any signs or symptoms of pancreatitis. Discontinue RYLAZE in patients with severe or hemorrhagic pancreatitis. In the case of mild pancreatitis, withhold RYLAZE until the signs and symptoms subside and amylase and/or lipase levels return to 1.5 times the ULN [see Dosage and Administration (2.3)]. After resolution of mild pancreatitis, treatment with RYLAZE may be resumed.

5.3 Thrombosis

Serious thrombotic events, including sagittal sinus thrombosis and pulmonary embolism, have been reported in 1% of patients following treatment with RYLAZE. Discontinue RYLAZE for a thrombotic event, and administer appropriate antithrombotic therapy. Consider resumption of treatment with RYLAZE only if the patient had an uncomplicated thrombosis [see Dosage and Administration (2.3)].

5.4 Hemorrhage

Bleeding was reported in 25% of patients treated with RYLAZE, and it was severe in 2%. Most commonly observed reactions were bruising (12%) and nose bleed (9%) [see Adverse Reactions (6.1)].

In patients treated with L-asparaginase class products, hemorrhage may be associated with increased prothrombin time (PT), increased partial thromboplastin time (PTT), and hypofibrinogenemia. Consider appropriate replacement therapy in patients with severe or symptomatic coagulopathy [see Dosage and Administration (2.3)].

5.5 Hepatotoxicity, including Hepatic Veno-Occlusive Disease

Elevated bilirubin and/or transaminases occurred in 75% of patients treated with RYLAZE in clinical trials, and 26% had Grade ≥ 3 elevations. Elevated bilirubin occurred in 28% of patients treated with RYLAZE in clinical trials, and 2% had Grade ≥ 3 elevations. Elevated transaminases occurred in 73% of patients treated with RYLAZE in clinical trials, and 25% had Grade ≥ 3 elevations [see Adverse Reactions (6.1)].

Hepatotoxicity, including severe, life-threatening, and potential fatal cases of hepatic veno-occlusive disease (VOD), have been observed in patients treated with asparaginase class products in combination with standard chemotherapy, including during the induction phase of multiphase chemotherapy [see Adverse Reactions (6)]. Do not administer RYLAZE to patients with severe hepatic impairment [see Contraindication (4)]. Inform patients of the signs and symptoms of hepatotoxicity.

Evaluate bilirubin and transaminases prior to each cycle of RYLAZE and at least weekly during cycles of treatment that include RYLAZE, through four weeks after the last dose of RYLAZE. Monitor frequently for signs and symptoms of hepatic VOD, which may include rapid weight gain, fluid retention with ascites, hepatomegaly (which may be painful), and rapid increase of bilirubin. For patients who develop abnormal liver tests after RYLAZE, more frequent monitoring for liver test abnormalities and clinical signs and symptoms of VOD is recommended. In the event of serious liver toxicity, including VOD, discontinue treatment with RYLAZE and provide supportive care [see Dosage and Administration (2.3)].

6 ADVERSE REACTIONS

The following clinically significant adverse reactions are described in greater detail in other sections of the labeling:

- Hypersensitivity Reactions [see Warnings and Precautions (5.1)]
- Pancreatic Toxicity [see Warnings and Precautions (5.2)]
- Thrombosis [see Warnings and Precautions (5.3)]
- Hemorrhage [see Warnings and Precautions (5.4)]
- Hepatotoxicity, including VOD [see Warnings and Precautions (5.5)]

6.1 Clinical Trials Experience

Because clinical trials are conducted under widely varying conditions, adverse reaction rates observed in the clinical trials of a drug cannot be directly compared to rates in the clinical trials of another drug and may not reflect the rates observed in practice.

The safety of RYLAZE described in the WARNINGS AND PRECAUTIONS reflect exposure in 167 patients administered RYLAZE intramuscularly at various dosages when used in combination with chemotherapy in study JZP458-201 [see Clinical Studies (14)]. These patients received a median of 4 courses of RYLAZE (range: 1-15 courses); 65% of patients received at least four courses.

The safety of RYLAZE described below and in Table 3 was evaluated in study JZP458-201, a multi-cohort study. Patients received RYLAZE administered intramuscularly at dosages of 25 mg/m^2 on Monday, Wednesday, and Friday or 25 mg/m^2 on Monday and Wednesday, and 50 mg/m^2 on Friday, for 6 doses as a replacement for a single dose of pegaspargase as a component of multi-agent chemotherapy [see Clinical Studies (14)]. The patients had a median age of 11 years (range: 1‑25 years); the majority of patients were male (57%) and White (68%). The patients received a median of 4 courses of RYLAZE (range: 1-14 courses); 65% of patients received at least four courses.

A fatal adverse reaction (infection) occurred in 1 patient treated with the RYLAZE 25/25/25 mg/m^2 dosage. Serious adverse reactions occurred in 60% of patients who received the recommended dosages of RYLAZE. The most frequent nonhematological serious adverse reactions (in ≥ 5% of patients) were febrile neutropenia, infection, drug hypersensitivity, pyrexia, nausea, dehydration, stomatitis, acute kidney injury, pancreatitis, diarrhea, and viral infection. Permanent discontinuation due to an adverse reaction occurred in 10% of patients who received RYLAZE intramuscularly at the recommended dosages. Adverse reactions resulting in permanent discontinuation included pancreatitis (5%), drug hypersensitivity (4%), and infection (1%).

All patients treated with the recommended dosages of RYLAZE as a component of multi-agent chemotherapy experienced neutropenia, anemia, or thrombocytopenia. The most common nonhematological adverse reactions (incidence > 20%) in patients were abnormal liver test, nausea, musculoskeletal pain, infection, fatigue, headache, febrile neutropenia, pyrexia, hemorrhage, stomatitis, abdominal pain, decreased appetite, drug hypersensitivity, hyperglycemia, diarrhea, pancreatitis, and hypokalemia. Table 3 shows the common adverse reactions occurring in at least 15% of the patients.

Table 3: Adverse Reactions (≥ 15% Incidence) in Patients Receiving RYLAZE as a Component of Multi-Agent Chemotherapy in Study JZP458-201
Adverse Reaction | RYLAZE; 25/25/25 mg/m^2; Intramuscular Dosagea; (N = 33) |  | RYLAZE; 25/25/50 mg/m^2; Intramuscular Dosagea; (N = 51)
Adverse Reaction | All Grades; (%) | Grades 3-4; (%) | All Grades; (%) | Grades 3-4; (%)
Abnormal liver test*# | 70 | 18 | 75 | 27
Musculoskeletal pain* | 45 | 6 | 35 | 4
Nausea* | 45 | 9 | 47 | 8
Fatigue* | 36 | 18 | 22 | 18
Headache | 36 | 0 | 22 | 0
Infection*b | 36 | 15 | 27 | 17
Febrile neutropenia | 30 | 30 | 27 | 27
Pyrexia | 30 | 6 | 20 | 0
Hemorrhage* | 24 | 0 | 27 | 6
Stomatitis | 24 | 12 | 27 | 4
Abdominal pain* | 21 | 0 | 25 | 2
Decreased appetite | 21 | 6 | 27 | 6
Drug hypersensitivity* | 21 | 6 | 24 | 2
Hyperglycemia | 21 | 3 | 12 | 4
Diarrhea* | 18 | 6 | 25 | 4
Tachycardia* | 18 | 0 | 16 | 2
Cough | 15 | 0 | 14 | 0
Dehydration | 15 | 9 | 12 | 6
Insomnia | 15 | 0 | 4 | 0
Peripheral neuropathy* | 15 | 0 | 6 | 0
Pancreatitis*# | 12 | 0 | 22 | 10
Hypokalemia | 9 | 3 | 22 | 8

* Includes grouped terms: Abnormal liver test: alanine aminotransferase increased, aspartate aminotransferase increased, blood bilirubin increased, transaminases increased; Musculoskeletal pain: arthralgia, back pain, musculoskeletal chest pain, musculoskeletal pain, myalgia, pain in extremity; Nausea: nausea, vomiting; Fatigue: fatigue, asthenia; Infection: sepsis, upper respiratory tract infection, enterocolitis infectious, skin infection, bacteremia, paronychia, pneumonia, otitis externa, soft tissue infection, abdominal infection, conjunctivitis, device related infection, folliculitis, lymph gland infection, necrotizing fasciitis, perirectal abscess, peritonsillar abscess, sinusitis, subcutaneous abscess, wound infection; Drug hypersensitivity: drug hypersensitivity, rash, infusion related reaction, lip swelling, periorbital edema, throat irritation, urticaria, dry skin, eczema, erythema, hand dermatitis, rash maculo-papular, rash papular; Hemorrhage: contusion, epistaxis, catheter site hemorrhage, petechiae, hematochezia, menorrhagia, mouth hemorrhage, increased tendency to bruise, rectal hemorrhage; Abdominal pain: abdominal pain, abdominal pain upper; Diarrhea: diarrhea, colitis; Tachycardia: sinus tachycardia, tachycardia; Peripheral neuropathy: peripheral motor neuropathy, neuropathy peripheral, peripheral sensory neuropathy; Pancreatitis: pancreatitis, pancreatitis acute, amylase increased, lipase increased.

*Includes adverse event terms and laboratory abnormalities
Grading is based on Common Terminology Criteria for Adverse Events version 5.0.

a RYLAZE was administered as a component of multi-agent chemotherapy regimens on a Monday, Wednesday, and Friday schedule.
b Does not include the following fatal adverse reactions: infection (N=1).

Clinically relevant adverse reactions in < 15% of patients who received RYLAZE in combination with chemotherapy included:

Gastrointestinal disorders: Abdominal discomfort, abdominal distension, constipation, gastritis

General disorders and administration site conditions: Infusion site reaction, injection site reaction, pain

Infections and infestations: Viral infection, bacterial infection, fungal infection

Investigations: Antithrombin III decreased, blood cholesterol increased, blood fibrinogen decreased, activated partial thromboplastin time prolonged

Metabolism and nutrition disorders: Acidosis, hyperammonemia, hyperphosphatemia, hypertriglyceridemia, hypoglycemia

Musculoskeletal and connective tissue disorders: Bone pain, muscular weakness, muscle spasms

Nervous system disorders: Paresthesia, dizziness, gait disturbance, hyperammonemic encephalopathy

Psychiatric disorders: Agitation, anxiety, irritability

Respiratory, thoracic, and mediastinal disorders: Acute respiratory distress syndrome, pulmonary edema

Renal and urinary disorders: Acute kidney injury

Skin and subcutaneous disorders: Pruritus

Vascular disorders: Hypertension, hypotension, thrombosis

6.2 Postmarketing Experience

The following adverse reactions have been identified during post approval use of RYLAZE. Because these reactions are reported voluntarily from a population of uncertain size, it is not always possible to reliably estimate their frequency or establish a causal relationship to drug exposure:

Hepatic: Veno-occlusive disease (VOD)

8 USE IN SPECIFIC POPULATIONS

8.1 Pregnancy

Risk Summary
Based on findings from animal reproduction studies, RYLAZE can cause fetal harm when administered to a pregnant woman. There are no available data on RYLAZE use in pregnant women to evaluate for a drug-associated risk of major birth defects, miscarriage, or adverse maternal or fetal outcomes. In animal reproductive and developmental toxicity studies, intramuscular administration of asparaginase Erwinia chrysanthemi to pregnant rats and rabbits during organogenesis resulted in structural abnormalities and embryo-fetal mortality (see Data) at exposures below those in patients at the recommended human dose. Advise pregnant women of the potential risk to a fetus.

In the U.S. general population, the estimated background risks of major birth defects and miscarriage in clinically recognized pregnancies are 2 to 4% and 15 to 20%, respectively.

Data
Animal Data
Animal reproductive and developmental toxicity studies have not been conducted with RYLAZE.

In embryofetal development studies, asparaginase Erwinia chrysanthemi was administered intramuscularly every other day during the period of organogenesis to pregnant rats (at 3, 6, or 12 mg/m^2) and rabbits (at 0.12, 0.30, or 0.48 mg/m^2). In rats given 12 mg/m^2 (approximately 0.48 times the maximum recommended human dose), maternal toxicity of decreased body weight gain was observed, as was a fetal finding of increased incidence of partially undescended thymic tissue. In rabbits, maternal toxicity consisting of decreased body weight was observed at 0.48 mg/m^2 (approximately 0.02 times the maximum recommended human dose). Increased post-implantation loss, a decrease in the number of live fetuses, and gross abnormalities (e.g., absent kidney, absent accessory lung lobe, additional subclavian artery, and delayed ossification) were observed at doses of ≥ 0.12 mg/m^2 (approximately 0.005 times the maximum recommended human dose).

8.2 Lactation

Risk Summary
There are no data on the presence of asparaginase erwinia chrysanthemi (recombinant)-rywn in human milk, the effects on the breastfed child, or the effects on milk production. Because of the potential for adverse reactions in the breastfed child, advise women not to breastfeed during treatment with RYLAZE and for 1 week after the last dose.

8.3 Females and Males of Reproductive Potential

RYLAZE can cause fetal harm when administered to a pregnant woman [see Use in Specific Populations (8.1)].

Pregnancy Testing
Pregnancy testing is recommended in females of reproductive potential prior to initiating RYLAZE.

Contraception
Advise females of reproductive potential to use effective non-hormonal contraceptive methods during treatment with RYLAZE and for 3 months after the last dose.

8.4 Pediatric Use

The safety and effectiveness of RYLAZE in the treatment of ALL and LBL have been established in pediatric patients 1 month to < 17 years who have developed hypersensitivity to a long-acting E. coli-derived asparaginase. Use of RYLAZE in these age groups is supported by evidence from an adequate and well-controlled study in adults and pediatric patients. The trial included 139 pediatric patients, including 2 infants (1 month to < 2 years), 99 children (2 years to < 12 years old), and 38 adolescents (12 years to < 17 years old). There were no clinically meaningful differences in safety or nadir serum asparaginase activity across age groups. The safety and effectiveness of RYLAZE have not been established in pediatric patients younger than 1 month of age.

8.5 Geriatric Use

Clinical studies of RYLAZE did not include sufficient numbers of patients 65 years of age and older to determine whether they respond differently from younger patients.

11 DESCRIPTION

Asparaginase erwinia chrysanthemi (recombinant)-rywn contains an asparagine specific bacterial enzyme (L-asparaginase). L-asparaginase is a tetrameric enzyme that consists of four identical 35 kDa subunits with a combined molecular weight of 140 kDa. The amino acid sequence is identical to native asparaginase Erwinia chrysanthemi (also known as crisantaspase). The activity of asparaginase erwinia chrysanthemi (recombinant)-rywn is expressed in units, defined as the amount of enzyme that catalyzes the conversion of 1μmol of L-asparagine per reaction minute, per mg of protein.

Asparaginase erwinia chrysanthemi (recombinant)-rywn is produced by fermentation of a genetically engineered Pseudomonas fluorescens bacterium containing the DNA which encodes for asparaginase Erwinia chrysanthemi.

RYLAZE (asparaginase erwinia chrysanthemi (recombinant)-rywn) injection is supplied as a sterile, clear to opalescent, colorless to slightly yellow, preservative-free solution for intramuscular injection. Each 0.5 mL contains 10 mg asparaginase erwinia chrysanthemi (recombinant)-rywn and the inactive ingredients: polysorbate 80 (0.1 mg), sodium chloride (1.5 mg), sodium phosphate dibasic anhydrous (0.8 mg), sodium phosphate monobasic monohydrate (0.6 mg), and trehalose dihydrate (32.1 mg). Sodium hydroxide may be added during manufacture to adjust the pH. The pH is approximately 7.

12 CLINICAL PHARMACOLOGY

12.1 Mechanism of Action

Asparaginase erwinia chrysanthemi (recombinant)-rywn is an enzyme that catalyzes the conversion of the amino acid L-asparagine into aspartic acid and ammonia. The pharmacological effect of RYLAZE is based on the killing of leukemic cells due to depletion of plasma asparagine. Leukemic cells with low expression of asparagine synthetase have a reduced ability to synthesize asparagine, and therefore depend on an exogenous source of asparagine for survival.

12.2 Pharmacodynamics

Asparaginase erwinia chrysanthemi (recombinant)-rywn exposure-response relationships and the time course of pharmacodynamic response are unknown.

12.3 Pharmacokinetics

The pharmacokinetic parameters of asparaginase erwinia chrysanthemi (recombinant)-rywn are presented based on serum asparaginase activity (SAA) after administration of RYLAZE in pediatric and young adult patients with ALL or LBL, unless otherwise specified. Asparaginase erwinia chrysanthemi (recombinant)-rywn maximum SAA (Cmax) and area under the SAA-time curve (AUC) increase proportionally over a dosage range from 12.5 to 50 mg/m^2 (0.25 to 1 times the maximum approved recommended dose of 50 mg/m^2). The simulated exposures for asparaginase erwinia chrysanthemi (recombinant)-rywn after administration of the approved recommended dosages in a virtual population are summarized in Table 4.

Table 4: Simulated RYLAZE Pharmacokinetic Parameters Based on SAA
PK Parameter | Geometric Mean (%CV) After Last Dose
 | 25 mg/m^2 Intramuscularly; Every 48 Hours | 25/25/50 mg/m^2 Intramuscularly; Monday, Wednesday, Friday
 | 25 mg/m^2 Intramuscularly; Every 48 Hours | Last 25 mg/m^2; Wednesday morning dose | Last 50 mg/m^2; Friday afternoon dose
Cmax (U/mL) | 2.3 (55%) | 2.3 (54%) | 4.1 (57%)
Ctrough (U/mL) | 0.46 (75%) | 0.3 (75%)a | 0.39 (87%)b

a Ctrough at maximum interval of 58 hours after the last 25 mg/m^2 Wednesday morning dose.
b Ctrough at maximum interval of 67 hours after the last 50 mg/m^2 Friday afternoon dose.

Absorption
The median (min, max) Tmax of asparaginase erwinia chrysanthemi (recombinant)-rywn after intramuscular administration is 12 (8, 24) hours. The mean absolute bioavailability after intramuscular administration is 37% in healthy subjects.

Distribution
The geometric mean (%CV) volume of distribution of asparaginase erwinia chrysanthemi (recombinant)-rywn is 1.37 L/m^2 (47%).

Elimination
The geometric mean (%CV) clearance of asparaginase erwinia chrysanthemi (recombinant)-rywn is 0.17 L/hour/m^2 (42%) and the apparent half-life is 15.9 (11%) hours.

Metabolism
Asparaginase erwinia chrysanthemi (recombinant)-rywn is expected to be metabolized into small peptides by catabolic pathways.

Specific Populations
There were no clinically significant differences in the pharmacokinetics of asparaginase erwinia chrysanthemi (recombinant)-rywn based on age (1.4 to 25 years), weight (9 to 131 kg), or sex after the dose was adjusted by body surface area (BSA). The effect of renal and hepatic impairment on the pharmacokinetics of asparaginase erwinia chrysanthemi (recombinant)-rywn has not been studied.

Body Surface Area
The volume of distribution and clearance of asparaginase erwinia chrysanthemi (recombinant)-rywn increase with increasing BSA (0.44 to 2.53 m^2).

Racial and Ethnic Groups
Black or African American patients had 29% lower clearance which may increase SAA exposure compared to White and Asian patients. There were no clinically significant differences in clearance between Hispanic and Non-Hispanic patients.

12.6 Immunogenicity

The observed incidence of anti-drug antibodies is highly dependent on the sensitivity and specificity of the assay. Differences in assay methods preclude meaningful comparisons of the incidence of anti‑drug antibodies in the studies described below with the incidence of anti-drug antibodies in other studies, including those of RYLAZE or of other asparaginase erwinia chrysanthemi (recombinant) products.

During treatment in Study JZP458-201 (range 1 to 15 courses), 78/166 (47%) of patients treated with RYLAZE intramuscularly developed anti-asparaginase erwinia chrysanthemi (recombinant)-rywn antibodies. The effects of anti-drug antibodies on pharmacokinetics, pharmacodynamics, and effectiveness have not been adequately characterized.

13 NONCLINICAL TOXICOLOGY

13.1 Carcinogenesis, Mutagenesis, Impairment of Fertility

Carcinogenicity, mutagenicity, and impairment of fertility studies have not been conducted with asparaginase erwinia chrysanthemi (recombinant)-rywn.

In a fertility and early embryonic development study in rats, asparaginase Erwinia chrysanthemi had no effect on male or female fertility when administered intramuscularly at doses of up to 12 mg/m^2 (approximately 0.48 times the maximum recommended human dose) every other day for a total of 35 doses. In males, decreased sperm count was observed at all doses but did not impact fertility.

14 CLINICAL STUDIES

The efficacy of RYLAZE for the treatment of patients with acute lymphoblastic leukemia (ALL) or lymphoblastic lymphoma (LBL) who have developed hypersensitivity to E. coli-derived asparaginase as a component of a multi-agent chemotherapeutic regimen was evaluated in Study JZP458-201 (NCT04145531), an open-label, multi-cohort, multi-center trial. In this trial, RYLAZE was administered at various dosages and routes of administration every Monday, Wednesday, and Friday for a total of 6 doses to replace each dose of pegaspargase.

For the 225 evaluable patients, the median age was 10 years (range: 1-25 years); 61% were male and 39% were female; 69% were White, 11% were Black/African American, 4% were Asian, and 16% were of other or unknown race: 187 (83%) patients had experienced a hypersensitivity reaction (Grade ≥ 3) to pegaspargase, and 15 patients (7%) reported silent inactivation.

The determination of efficacy was based on a demonstration of the achievement and maintenance of nadir serum asparaginase activity (NSAA) above the level of 0.1 U/mL by simulation. Table 5 shows the proportion with NSAA ≥ 0.1 U/mL for each approved dosage regimen based on simulation in a virtual population [see Clinical Pharmacology (12.3)].

Table 5: Proportion (95% CI) with NSAA ≥ 0.1 U/mL by Simulation
RYLAZE Dosage | Trough Sampling Time | Proportion with; NSAA > 0.1 U/mL (95% CI)a
25 mg/m^2 intramuscularly every 48 hours | 48 hours | 96.0 (94.4, 97.2)
25/25/50 mg/m^2 intramuscularly Monday morning/Wednesday morning/Friday afternoon | Friday afternoon: 58 hours after 25 mg/m^2 Wednesday morning doseb | 91.6 (90.4, 92.8)
25/25/50 mg/m^2 intramuscularly Monday morning/Wednesday morning/Friday afternoon | Monday morning: 67 hours after 50 mg/m^2 Friday afternoon dosec | 91.4 (90.1, 92.6)

a Based on 2,000 virtual subjects.
b Based on maximum interval of 58 hours between the Wednesday morning and Friday afternoon doses.
c Based on maximum interval of 67 hours between the Friday afternoon and Monday morning doses.

16 HOW SUPPLIED/STORAGE AND HANDLING

RYLAZE (asparaginase erwinia chrysanthemi (recombinant)-rywn) injection is supplied as a sterile, clear to opalescent, colorless to slightly yellow, preservative-free solution in single-dose vials. Each single-dose vial (NDC 68727-900-01) contains 10 mg/0.5 mL asparaginase erwinia chrysanthemi (recombinant)-rywn. Each carton of RYLAZE (NDC 68727-900-03) contains 3 single-dose vials.

Store RYLAZE vials refrigerated at 2°C to 8°C (36°F to 46°F) in the original carton to protect from light. Do not shake or freeze.

17 PATIENT COUNSELING INFORMATION

- Hypersensitivity
  Inform patients of the risk of allergic reactions, including anaphylaxis. Instruct the patient on the symptoms of allergic reactions and to seek medical advice immediately if they experience such symptoms [see Warnings and Precautions (5.1)].
- Pancreatitis
  Instruct patients on signs and symptoms of pancreatitis and to seek medical attention if they experience severe abdominal pain [see Warnings and Precautions (5.2)].
- Thrombosis
  Instruct patients on the risk of thrombosis and to seek medical advice immediately if they experience headache, arm or leg swelling, shortness of breath, and chest pain [see Warnings and Precautions (5.3)].
- Hemorrhage
  Advise patients to report any unusual bleeding or bruising to their healthcare provider [see Warnings and Precautions (5.4)].
- Hepatotoxicity, including Veno-Occlusive Liver Disease
  Inform patients that liver problems, including severe, life-threatening, or fatal VOD and abnormalities in liver tests, may develop during RYLAZE treatment. Advise patients to report any jaundice, severe nausea or vomiting, or easy bleeding or bruising to their healthcare provider [see Warnings and Precautions (5.5)].
- Pregnancy
  Advise pregnant women of the potential risk to a fetus. Advise females of reproductive potential to inform their healthcare provider of a known or suspected pregnancy [see Use in Specific Populations (8.1)].
Advise females of reproductive potential to use effective non-hormonal contraception during treatment with RYLAZE and for 3 months after the last dose [see Use in Specific Populations (8.3)].
- Lactation
  Advise women not to breastfeed during treatment with RYLAZE and for 1 week after the last dose [see Use in Specific Populations (8.2)].

Manufactured by:
Jazz Pharmaceuticals Ireland Limited
Dublin, Ireland
U.S. License No. 2167

Distributed by:
Jazz Pharmaceuticals, Inc.
Palo Alto, CA 94306

Protected by U.S. Patent nos. 8,288,127 and 10,787,671

RYLAZE® is a trademark of Jazz Pharmaceuticals plc or its subsidiaries.

©2024 Jazz Pharmaceuticals

Package/Label Display Panel

3 vials (NDC 68727-900-01)
1 carton (NDC 68727-900-03)
asparaginase erwinia chrysanthemi (recombinant)-rywn
RYLAZE™
Injection, for intramuscular use
10 mg/0.5 mL